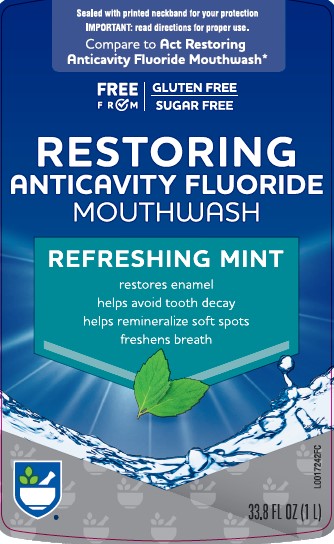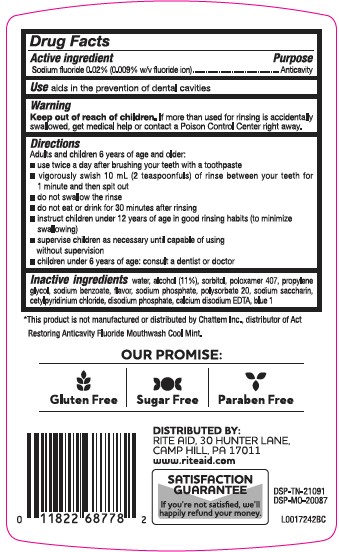 DRUG LABEL: Anticavity
NDC: 11822-6877 | Form: MOUTHWASH
Manufacturer: Rite Aid Corporation
Category: otc | Type: HUMAN OTC DRUG LABEL
Date: 20260130

ACTIVE INGREDIENTS: SODIUM FLUORIDE 0.2 mg/1 mL
INACTIVE INGREDIENTS: WATER; ALCOHOL; SORBITOL; POLOXAMER 407; PROPYLENE GLYCOL; SODIUM BENZOATE; SODIUM PHOSPHATE; POLYSORBATE 20; SACCHARIN SODIUM; CETYLPYRIDINIUM CHLORIDE; SODIUM PHOSPHATE, DIBASIC, ANHYDROUS; EDETATE CALCIUM DISODIUM ANHYDROUS; FD&C BLUE NO. 1

Rite Aid 581.000/581AA-AB
Restoring Anticavity Fluoride Mouthwash

Active ingredient

Sodium Fluoride 0.02% (0.009% w/v fluoride ion)

Purpose

Anticavity

Use

Aids in the prevention of dental cavities

Warnings

For this product

Keep out of reach of children.

If more than used for rinsing is accidentally swallowed, get medical help or contact a Poison Control Center right away.

Directions

Adults and children 6 years of age and older:

- use twice a day after brushing your teeth with a toothpaste
- vigorously swish 10 mL (2 teaspoonfuls) of rinse between your teeth for 1 minute and then spit out
- do not swallow the rinse
- do not eat or drink for 30 minutes after rinsing
- instruct children under 12 years of age in good rinsing habits (to minimize swallowing)
- supervise children as necessary until capable of using without supervision
- children under 6 years of age: consult a dentist or doctor

Inactive ingredients

water, alcohol (11%), sorbitol, poloxamer 407, propylene glycol, sodium benzoate, flavor, sodium phosphate, polysorbate 20, sodium saccharin, cetylpyridinium chloride, disodium phosphate, calcium disodium EDTA, blue 1

Disclaimer

*This product is not manufactured or distributed by Chattem, Inc., distributor of Act Restoring Anticavity Fluoride Mouthwash Cool Mint.

Claims

OUR PROMISE:

Gluten Free

Sugar Free

Paraben Free

Adverse Reaction

DISTRIBUTED BY:

RITE AID, 30 HUNTER LANE,

CAMPHILL, PA 17011

www.riteaid.com

SATISFACTION GUARANTEE

If you're not satisfied, we'll happily refund your money.

DSP-TN-21091

DSP-MO-20087

principal display panel

Sealed with printed neckband for your protection

IMPORTANT: read directions for proper use.

Compare to Act Restoring Anticavity Fluoride Mouthwash*

FREE FROM

GLUTEN FREE

SUGAR FREE

RESTORING

ANTICAVITY FLUORIDE

MOUTHWASH

REFRESHING MINT

restores enamel

helps avoid tooth decay

helps remineralize soft spots

freshens breath

33.8 FL OZ (1 L)